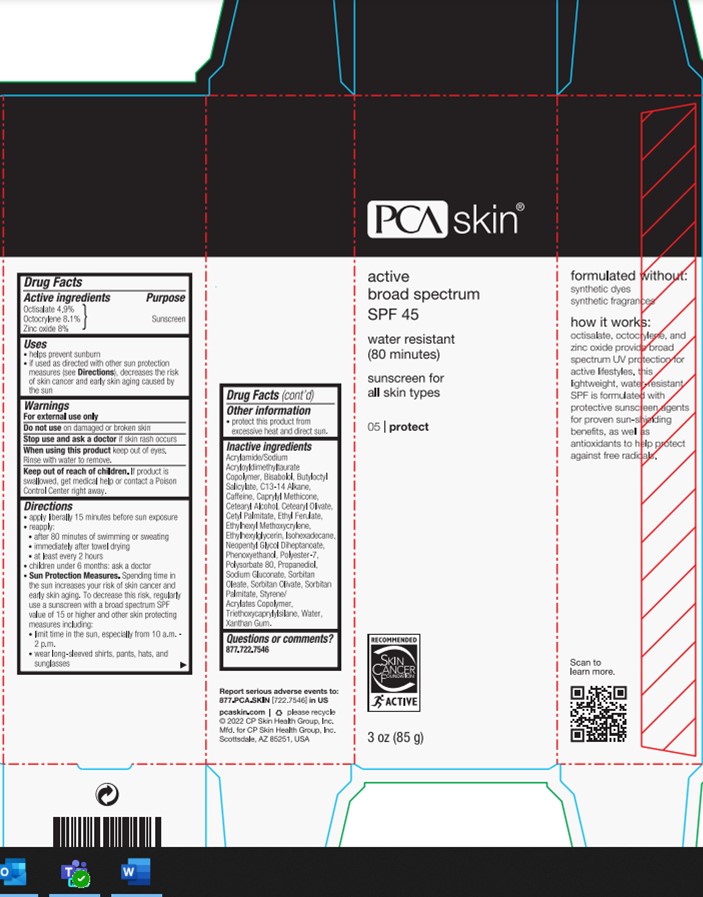 DRUG LABEL: Active
NDC: 68726-264 | Form: LOTION
Manufacturer: CP Skin Health Group, Inc.
Category: otc | Type: HUMAN OTC DRUG LABEL
Date: 20240214

ACTIVE INGREDIENTS: OCTOCRYLENE 8.5 g/100 g; ZINC OXIDE 8 g/100 g; OCTISALATE 5 g/100 g
INACTIVE INGREDIENTS: PROPANEDIOL; PHENOXYETHANOL; ETHYLHEXYLGLYCERIN; NEOPENTYL GLYCOL DIHEPTANOATE; TRIETHOXYCAPRYLYLSILANE; SORBITAN OLIVATE; CETYL PALMITATE; SORBITAN MONOPALMITATE; SORBITAN MONOOLEATE; ETHYLHEXYL METHOXYCRYLENE; POLYESTER-7; WATER; ISOHEXADECANE; XANTHAN GUM; CAFFEINE; CAPRYLYL TRISILOXANE; LEVOMENOL; SODIUM GLUCONATE; ETHYL FERULATE; STYRENE/ACRYLAMIDE COPOLYMER (MW 500000); BUTYLOCTYL SALICYLATE; CETEARYL OLIVATE; CETOSTEARYL ALCOHOL; POLYSORBATE 80

PCA Skincare Active Broad Spectrum SPF 45

Active ingredients

Octisalate 4.9%, Octocrylene 8.1%, Zinc Oxide 8%

Purpose

Sunscreen

Uses

Helps prevent sunburn

If used as directed with other sun protection measures (see Direction), decreases the risk of skin cancer and early skin aging caused by the sun.

Warnings

For external use only

Do not use on damaged or broken skin

Stop use and ask a doctor if skin rash occurs.

When using this product keep out of eyes. Rinse with water to remove.

Keep out of reach of children. If product is swallowed, get medical help or contact a Poison Control Center right away.

Directions

Apply liberally 15 minutes before sun exposure

Reapply:

- after 80 minutes of swimming or sweating

- immediately after towel drying

- at least every 2 hours

Children under 6 months: ask a doctor

Sun Protection Measures. Spending time in the sun increases your risk of skin cancer and early skin aging. To decrease this risk, regularly use a sunscreen with a borad specturm SPF value of 15 or higher and other skin protecting measures including:

- limit time in the sun, specially from 10a.m. - 2 p.m.

- weare long-sleeved shirts, pants, hats, and sunglasses

Other information

Protect this product from excessive heat and direct sun.

Inactive Ingredients

Acrylamide/Sodium Acryloyldimethyltaurate Copolymer
Bisabolol
Butyloctyl Salicylate
C13-14 Alkane
Caffeine
Caprylyl Methicone
Cetearyl Alcohol
Cetearyl Olivate
Cetyl Palmitate
Ethyl Ferulate
Ethylhexyl Methoxycrylene
Ethylhexylglycerin
Isohexadecane
Neopentyl Glycol Diheptanoate
Phenoxyethanol
Polyester-7
Polysorbate 80
Propanediol
Sodium Gluconate
Sorbitan Oleate
Sorbitan Olivate
Sorbitan Palmitate
Styrene/Acrylates Copolymer
Triethoxycaprylylsilane
Water
Xanthan Gum

Questions or comments?

877.722.7546